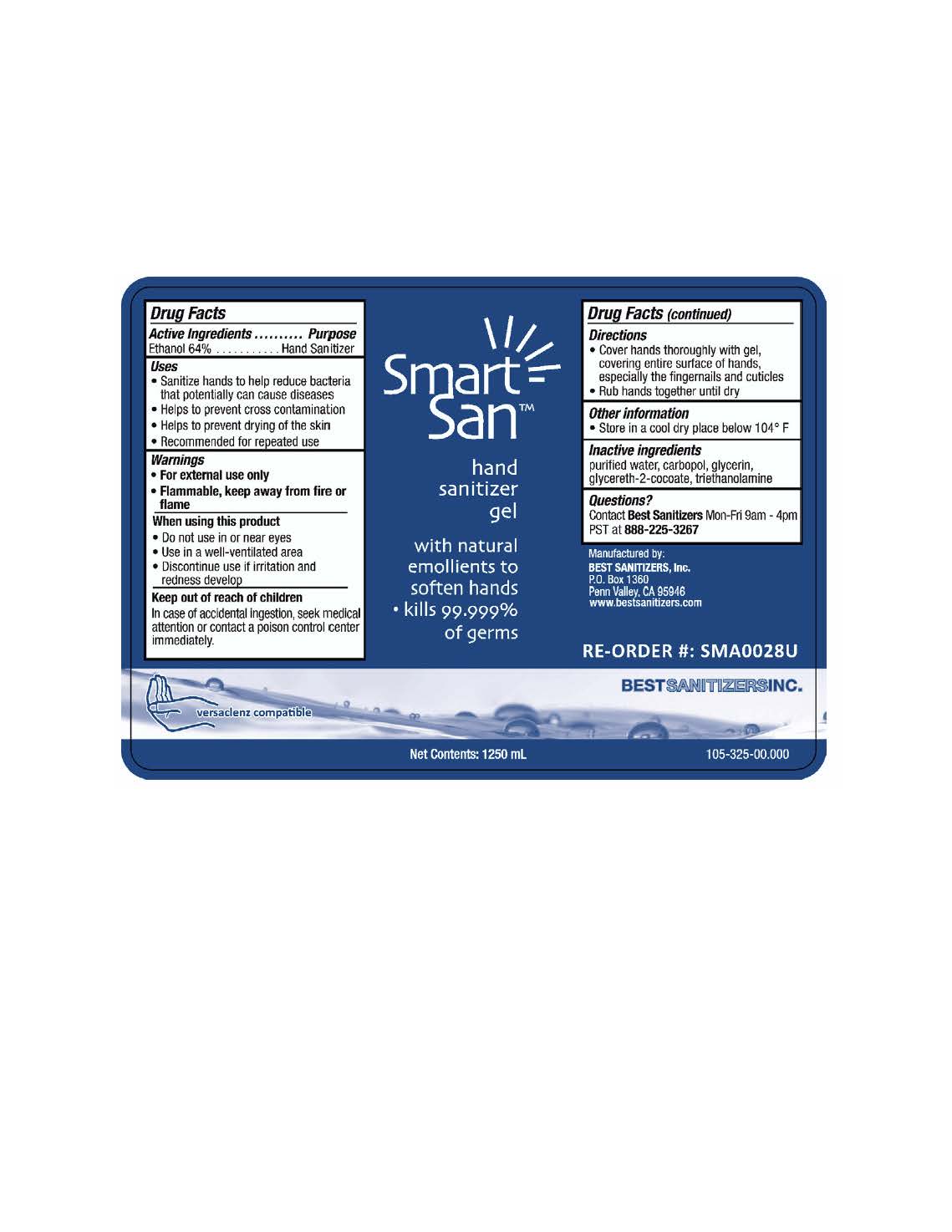 DRUG LABEL: SMART SAN HAND SANITIZER
NDC: 59900-129 | Form: LIQUID
Manufacturer: Best Sanitizers, Inc.
Category: otc | Type: HUMAN OTC DRUG LABEL
Date: 20241205

ACTIVE INGREDIENTS: ALCOHOL 64 mL/100 mL
INACTIVE INGREDIENTS: WATER; CARBOXYPOLYMETHYLENE; GLYCERIN; GLYCERETH-2 COCOATE; TROLAMINE

Drug Facts 59900-129

Active ingredients

Ethanol 64%

Purpose

Hand Sanitizer

Uses

- Sanitize hands to help reduce bacteria that potentially can cause diseases

- Helps to prevent cross contamination

- Helps to prevent drying of the skin

- Recommended for repeated use

Warnings

- For external use only

- Flammable, keep away from fire or flame

When using this product

- Do not use in or near eyes

- Use in well-ventilated area

- Discontinue use if irritation and redness develop

Keep out of reach of children

In case of accidental ingestion, seek medical attention or contact a poison control center immediately.

Directions

- Cover hands thoroughly with gel, covering entire surface of hands, especially the fingernails and cuticles

- Rub hands together until dry

Other information

- Store in a cool dry place below 104oF

Inactive ingredients

purified water, carbopol, glycerin, glycereth-2-cocoate, triethanolamine

Questions?

Contact Best SanitizersMon-Fri 9am - 4pm PST at 888-225-3267

PACKAGE LABEL

Smart

San

hand

sanitizer

gel

with natural

emollients to

soften hands

kills 99.999%

of germs

Net Contents: 1250 mL